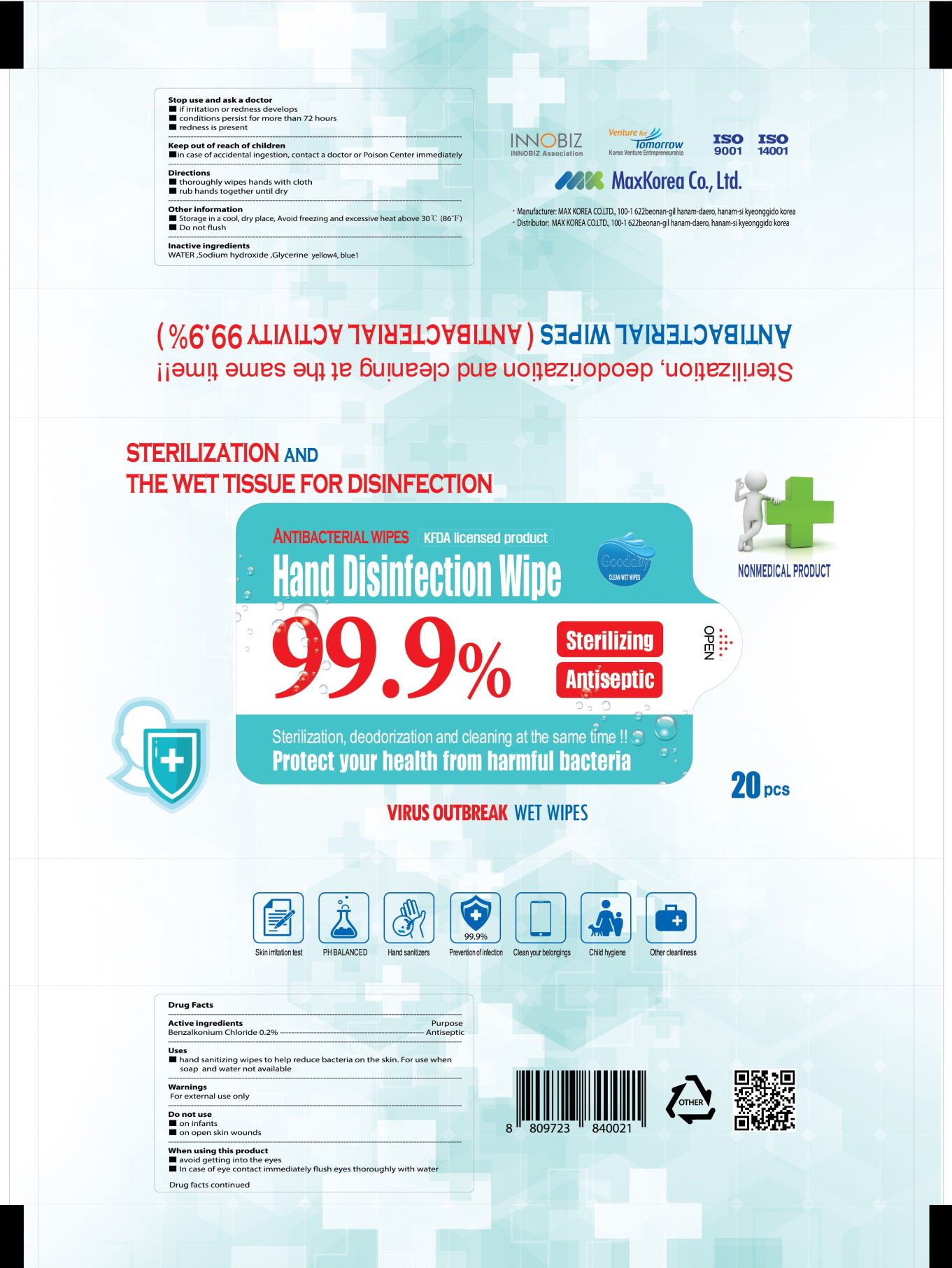 DRUG LABEL: Goodday Clean Wet Wipes
NDC: 79907-010 | Form: CLOTH
Manufacturer: Maxkorea Co., Ltd.
Category: otc | Type: HUMAN OTC DRUG LABEL
Date: 20200729

ACTIVE INGREDIENTS: Benzalkonium Chloride 0.2 1/100 1
INACTIVE INGREDIENTS: Water; SODIUM HYDROXIDE; Glycerin

ACTIVE INGREDIENT

Benzalkonium Chloride 0.2%

INACTIVE INGREDIENTS

Water, Sodium hydroxide, Glycerin, Yellow 4, Blue 1

PURPOSE

Antiseptic

WARNINGS

For external use only
--------------------------------------------------------------------------------------------------------
Do not use
■ on infants
■ on open skin wounds
--------------------------------------------------------------------------------------------------------
When using this product
■ avoid getting into the eyes
■ In case of eye contact immediately flush eyes thoroughly with water
--------------------------------------------------------------------------------------------------------
Stop use and ask a doctor
■ if irritation or redness develops
■ conditions persist for more than 72 hours
■ redness is present

KEEP OUT OF REACH OF CHILDREN

■ in case of accidental ingestion, contact a doctor or Poison Center immediately

Uses

■ hand sanitizing wipes to help reduce bacteria on the skin. For use when soap and water not available

Directions

■ thoroughly wipes hands with cloth
■ rub hands together until dry

Other information

■ Storage in a cool, dry place, Avoid freezing and excessive heat above 30 ℃ (86 ℉)
■ Do not flush